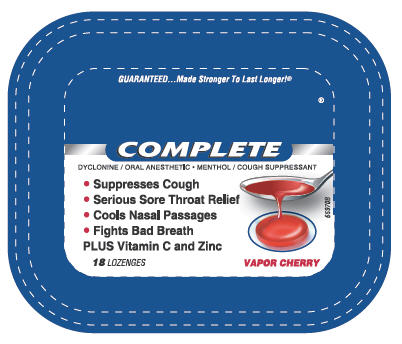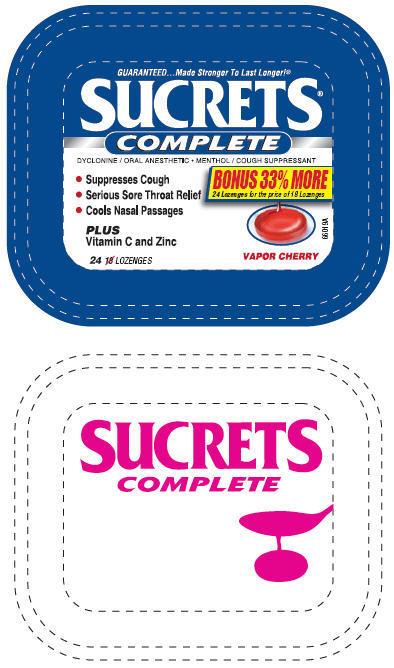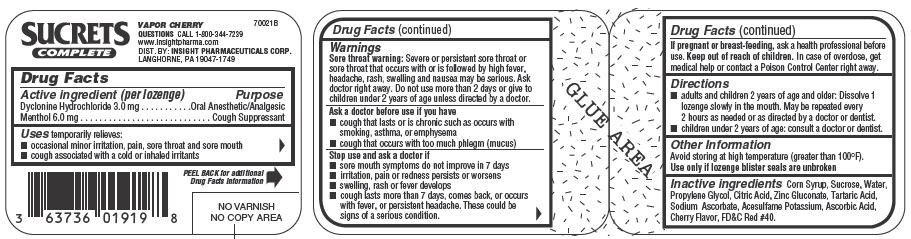 DRUG LABEL: Sucrets Complete
NDC: 63736-920 | Form: LOZENGE
Manufacturer: Insight Pharmaceuticals
Category: otc | Type: HUMAN OTC DRUG LABEL
Date: 20090804

ACTIVE INGREDIENTS: Dyclonine Hydrochloride 3 mg/1 1; Menthol 6 mg/1 1
INACTIVE INGREDIENTS: Corn Syrup; Sucrose; Water; Propylene Glycol; Citric Acid Monohydrate; Zinc Gluconate; Tartaric Acid; Sodium Ascorbate; Acesulfame Potassium; Ascorbic Acid; FD&C Red  no. 40

SUCRETS
COMPLETE

Active ingredient (per lozenge)

Dyclonine Hydrochloride 3.0 mg

Menthol 6.0 mg

Purpose

Oral Anesthetic/Analgesic

Cough Suppressant

Uses

temporarily relieves:

- occasional minor irritation, pain, sore throat and sore mouth
- cough associated with a cold or inhaled irritants

Warnings

Sore throat warning

Severe or persistent sore throat or sore throat that occurs with or is followed by high fever, headache, rash, swelling and nausea may be serious. Ask doctor right away. Do not use more than 2 days or give to children under 2 years of age unless directed by a doctor.

Ask a doctor before use if you have

- cough that lasts or is chronic such as occurs with smoking, asthma, or emphysema
- cough that occurs with too much phlegm (mucus)

Stop use and ask a doctor if

- sore mouth symptoms do not improve in 7 days
- irritation, pain or redness persists or worsens
- swelling, rash or fever develops
- cough lasts more than 7 days, comes back, or occurs with fever, or persistent headache. These could be signs of a serious condition.

PREGNANCY OR BREAST FEEDING

If pregnant or breast-feeding, ask a health professional before use.

Keep out of reach of children. In case of overdose, get medical help or contact a Poison Control Center right away.

Directions

- adults and children 2 years of age and older: Dissolve 1 lozenge slowly in the mouth. May be repeated every 2 hours as needed or as directed by a doctor or dentist.
- children under 2 years of age: consult a doctor or dentist.

Other Information

Avoid storing at high temperature (greater than 100°F).
Use only if lozenge blister seals are unbroken

Inactive ingredients

Corn Syrup, Sucrose, Water, Propylene Glycol, Citric Acid, Zinc Gluconate, Tartaric Acid, Sodium Ascorbate, Acesulfame Potassium, Ascorbic Acid, Cherry Flavor, FD&C Red #40.

QUESTIONS

CALL 1-800-344-7239
www.insightpharma.com

DIST. BY: INSIGHT PHARMACEUTICALS CORP.
LANGHORNE, PA 19047-1749

PRINCIPAL DISPLAY PANEL - 18 Lozenges Container

GUARANTEED...Made Stronger To Last Longer!®

SUCRETS®
COMPLETE

DYCLONINE / ORAL ANESTHETIC • MENTHOL / COUGH SUPPRESSANT

- Suppresses Cough
- Serious Sore Throat Relief
- Cools Nasal Passages
- Fights Bad Breath

PLUS Vitamin C and Zinc

18 LOZENGES

VAPOR CHERRY

65970B

PRINCIPAL DISPLAY PANEL - 24 Lozenges Container

GUARANTEED...Made Stronger To Last Longer!®

SUCRETS®
COMPLETE

DYCLONINE / ORAL ANESTHETIC • MENTHOL / COUGH SUPPRESSANT

- Suppresses Cough
- Serious Sore Throat Relief
- Cools Nasal Passages
  PLUS
  Vitamin C and Zinc

BONUS 33% MORE
24 Lozenges for the price of 18 Lozenges

24 LOZENGES

VAPOR CHERRY

66019A